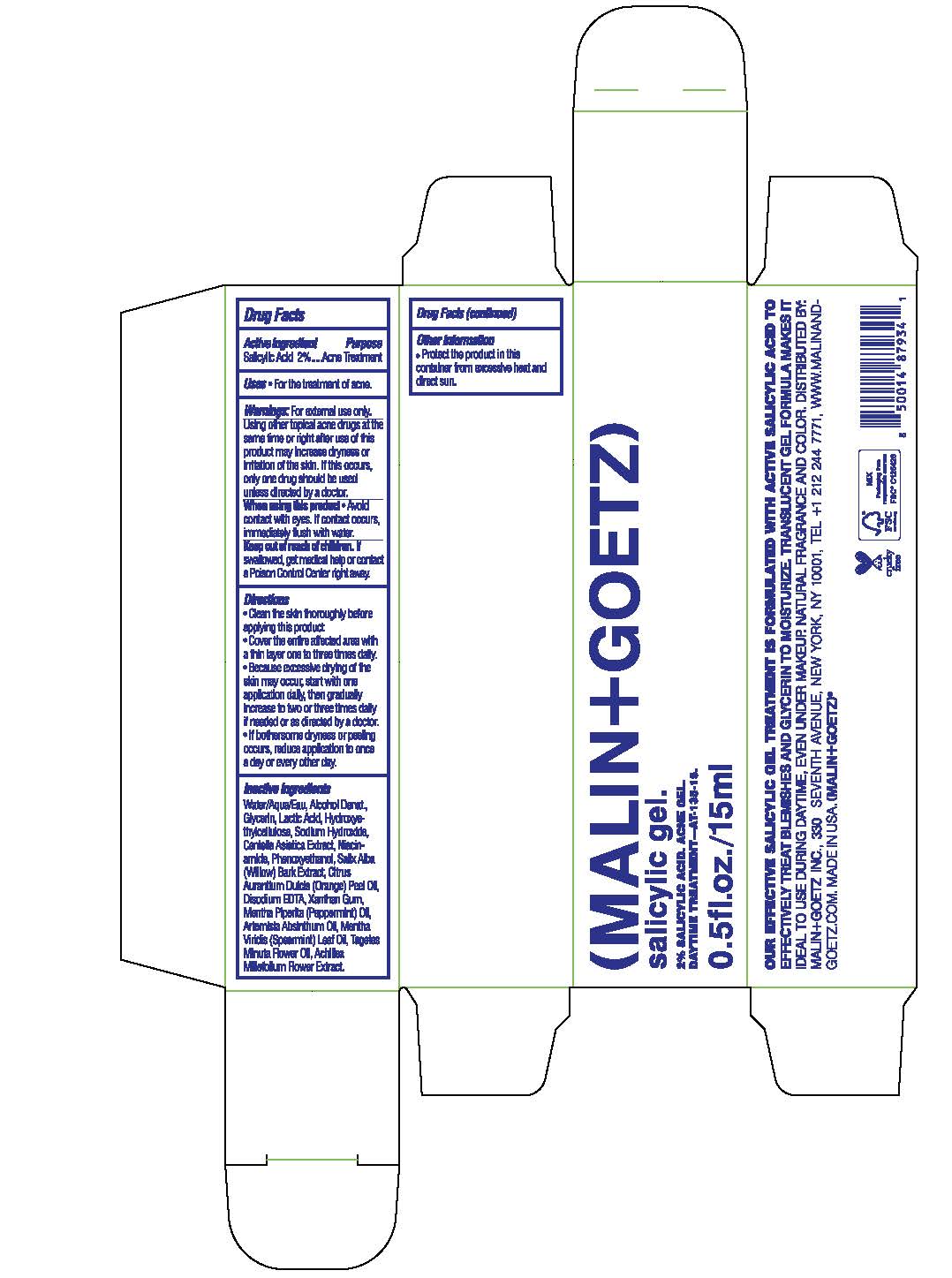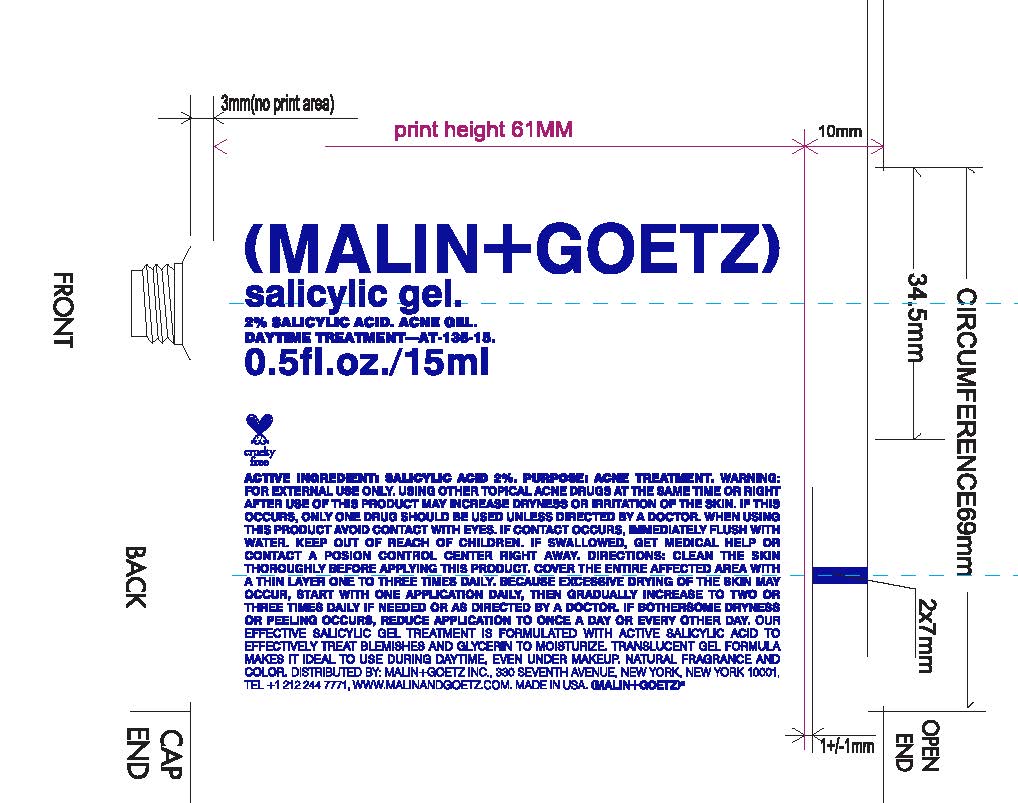 DRUG LABEL: salicylic gel
NDC: 53634-153 | Form: GEL
Manufacturer: Malin and Goetz Inc
Category: otc | Type: HUMAN OTC DRUG LABEL
Date: 20221123

ACTIVE INGREDIENTS: SALICYLIC ACID 2 g/100 mL
INACTIVE INGREDIENTS: SALIX ALBA BARK; PHENOXYETHANOL; EDETATE DISODIUM ANHYDROUS; XANTHAN GUM; PEPPERMINT OIL; TAGETES MINUTA FLOWER OIL; CENTELLA ASIATICA TRITERPENOIDS; ORANGE OIL, COLD PRESSED; LACTIC ACID; WATER; ALCOHOL; GLYCERIN; HYDROXYETHYL CELLULOSE, UNSPECIFIED; SODIUM HYDROXIDE; NIACINAMIDE; WORMWOOD OIL; SPEARMINT OIL; ACHILLEA MILLEFOLIUM FLOWER

salicylic gel

Active Ingredient Purpose

Salicylic Acid 2%--------Acne Treatment

Uses

For external use only

Keep out of reach of children.

If swallowed, get medical help or contact a Poison Control Center right away.

Warnings:

For external use only.

When using this product

Avoid contact with eyes. If contact occurs, immediately flush with water.

Directions

- Clean the skin thoroughly before applying this product
- Cover the entire affected area with a thin layer one to three times daily.
- Because excessive drying of the skin may occur, start with one application daily, then gradually increase totwo oe three times daily if needed or as directed by a doctor.
- If bothersome dryness or peeling occurs, reduce application to once a day or every other day.

Inactive ingredients

Water/Aqua/Eau, Alcohol Denat., Glycerin, Lactic Acid, Hydroxyethylcellulose, Sodium Hydroxide, Centella Asiatica Extract, Niacinamide, Phenoxyethanol, Salix Alba (Willow) Bark Extract, Citrus Aurantium Dulcis (Orange) Peel Oil, Disodium EDTA, Xanthan Gum, Mentha Piperita (Peppermint) Oil, Artemisia Absinthum Oil, Mentha Viridis (Spearmint) Leaf Oil, Tagetes Minuta Flower Oil, Achillea Millefolium Flower Extract.

Other Information

Protect the product in this container from excessive heat and direct sun.

INDICATIONS AND USAGE

Using other topical acne drugs at the same time or right after use of this product may increase dryness or irritation of the skin. If this occurs, only one drug should be used unless directed by a doctor.

PACKAGE LABEL

(MALIN+GOETZ)

salicylic gel.

2% Salicylic Acid. Acne Gel

Daytime Treatment

0.5fl.oz./15ml